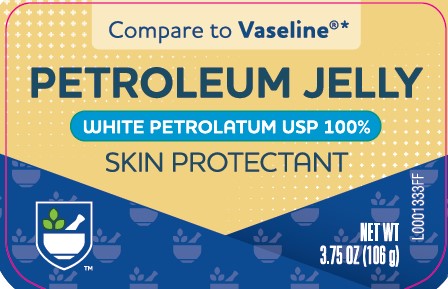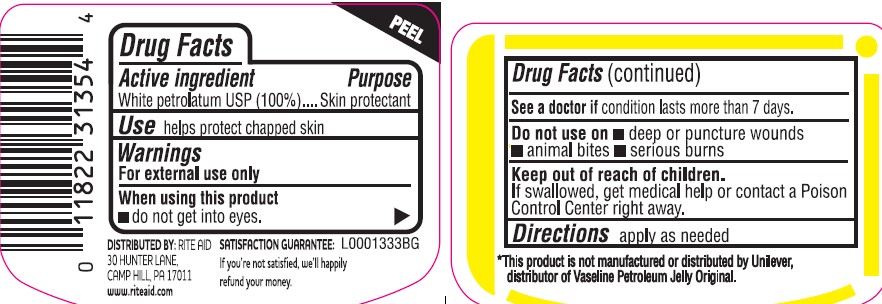 DRUG LABEL: Pure petroleum
NDC: 11822-3135 | Form: JELLY
Manufacturer: Rite Aid Corporation
Category: otc | Type: HUMAN OTC DRUG LABEL
Date: 20260130

ACTIVE INGREDIENTS: PETROLATUM 1 g/1 g

Rite Aid 069.001/069AA
Petroleum Jelly

Active ingredients

White Petrolatum USP (100%)

Purpose

Skin protectant

Use

helps protect chapped skin

Warnings

For external use only

When using this product

- do not get into eyes

See a doctor if

condition lasts more than 7 days.

Do not use on

- deep or puncture wounds
- animal bites
- serious burns

Keep out of reach of children.

If swallowed, get medical help or contact a Poison Control Center right away.

Directions

apply as needed

Inactive Ingredients

None

Dislcaimer

*This product is not manufactured or distributed by Unilever, distributor of Vaseline Petroleum Jelly Original.

Adverse reactions

DISTRIBUTED BY: RITE AID

30 HUNTER LANE

CAMP HILL, PA 17011

www.riteaid.com

SATISFACTION GUARANTEE

If you're not satisfied, we'll happily refund your money.

Principal display panel

Compare to Vaseline®*

PETROLEUM JELLY

WHITE PETROLATUM USP 100%

SKIN PROTECTANT

NET WT 3.75 (106 g)